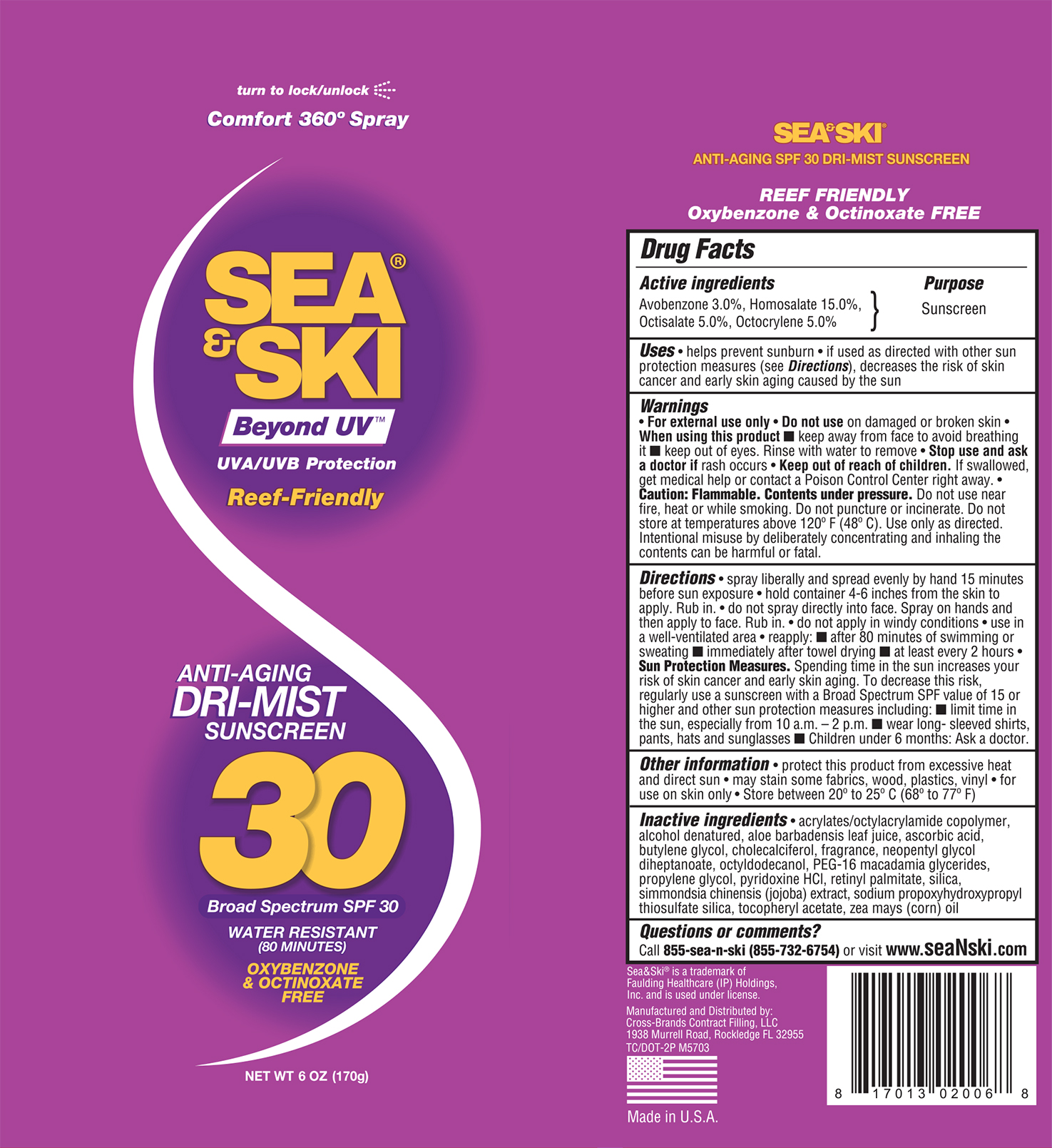 DRUG LABEL: Sea and Ski SPF 30 C-Spray
NDC: 73440-2006 | Form: AEROSOL, SPRAY
Manufacturer: Cross Brands Contract Filling
Category: otc | Type: HUMAN OTC DRUG LABEL
Date: 20210219

ACTIVE INGREDIENTS: AVOBENZONE 5.1 g/170 g; OCTISALATE 8.5 g/170 g; OCTOCRYLENE 8.5 g/170 g; HOMOSALATE 25.5 g/170 g
INACTIVE INGREDIENTS: ALCOHOL 108.5 g/170 g

Sea & Ski SPF 30 C-Spray